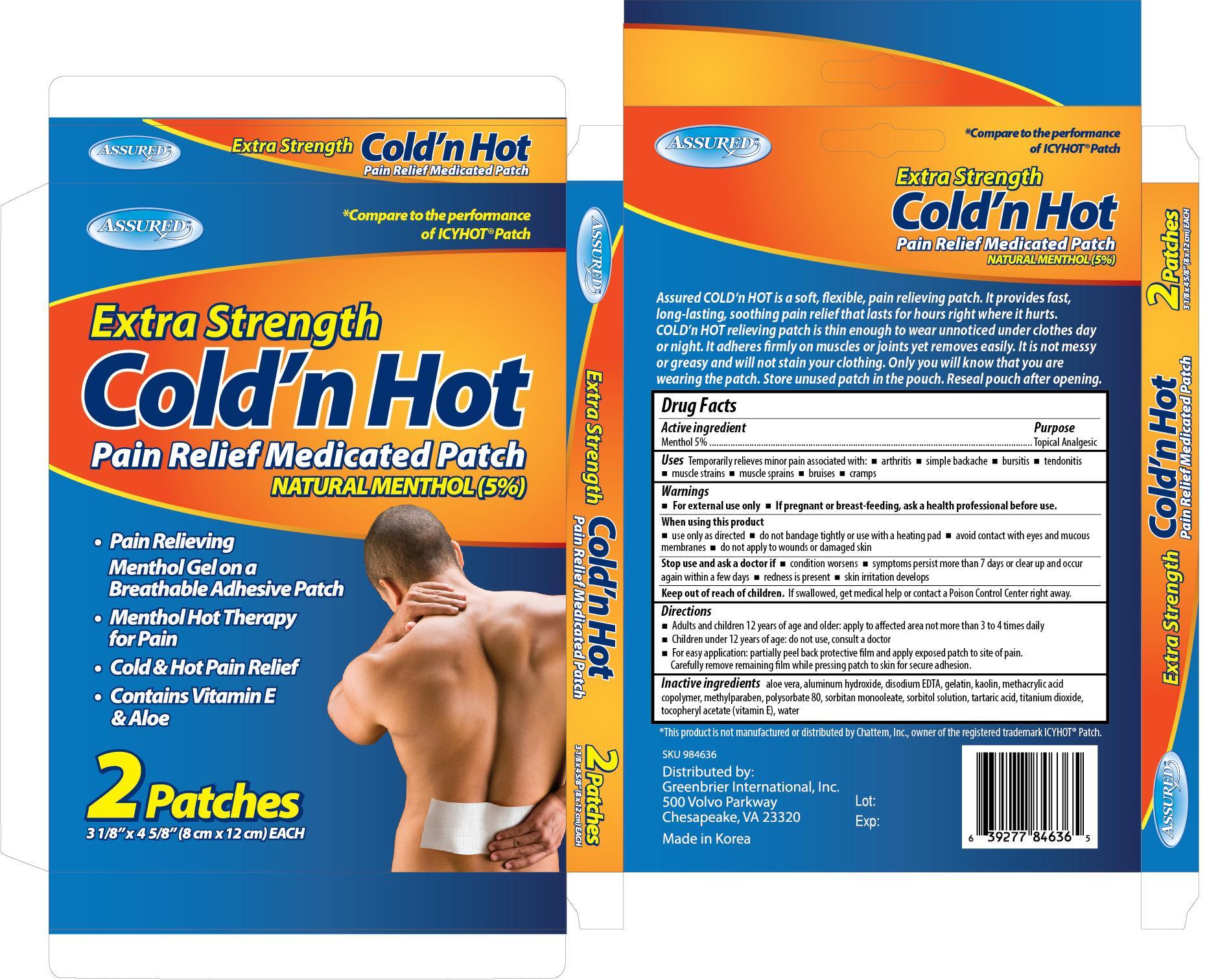 DRUG LABEL: Assured Extra Strength Cold n hot
                
NDC: 33992-8463 | Form: PATCH
Manufacturer: Greenbrier International, Inc.
Category: otc | Type: HUMAN OTC DRUG LABEL
Date: 20130630

ACTIVE INGREDIENTS: MENTHOL 750 mg/1 1
INACTIVE INGREDIENTS: ALOE VERA LEAF; ALUMINUM HYDROXIDE; EDETATE DISODIUM; GELATIN; KAOLIN; METHACRYLIC ACID - METHYL METHACRYLATE COPOLYMER (1:1); METHYLPARABEN; POLYSORBATE 80; SORBITAN MONOOLEATE; SORBITOL; TARTARIC ACID; TITANIUM DIOXIDE; WATER

Drug Facts

Active ingredient Purpose

Menthol 5%.....................................................Topical Analgesic

PURPOSE

Uses Temporarily relieves minor pain associated with:

- arthritis
- simple backache
- bursitis
- tendonitis
- muscle strains
- muscle sprains
- bruises
- cramps

Warnings

- For external use only
- If pregnant or breast-feeding, ask a health professional before use

When using this product

- use only as directed
- do not bandage tightly or use with a heating pad
- avoid contact with eyes and mucous membranes
- do not apply to wounds or damaged skin

Stop use and ask a doctor if

- condition worsens
- symptoms persist more than 7 days or clear up and occur again within a few days
- redness is present
- skin irritation develops

Keep out of reach of children. If swallowed, get medical help or contact a Poison Control Center right away.

Directions

- Adults and children 12 years of age and older: apply to affected area not more than 3 to 4 times daily
- Children under 12 years of age: do not use, consult a doctor
- For easy application: partially peel back protective film and apply exposed patch to site of pain. Carefully remove remaining film while pressing patch to skin for secure adhesion.

INACTIVE INGREDIENT

Inactive ingredients aloe vera, aluminum hydroxide, disodium EDTA, gelatin, kaolin, methacrylic acid copolymer, methylparaben, polysorbate 80, sorbitan monooleate, sorbitol solution, tartaric acid, titanium dioxide, tocopheryl acetate (vitamin E), water

DOSAGE AND ADMINISTRATION

Distributed by:

Greenbrier International, Inc.

500 Volvo Parkway

Chesapeake, VA 23320

Made in Korea